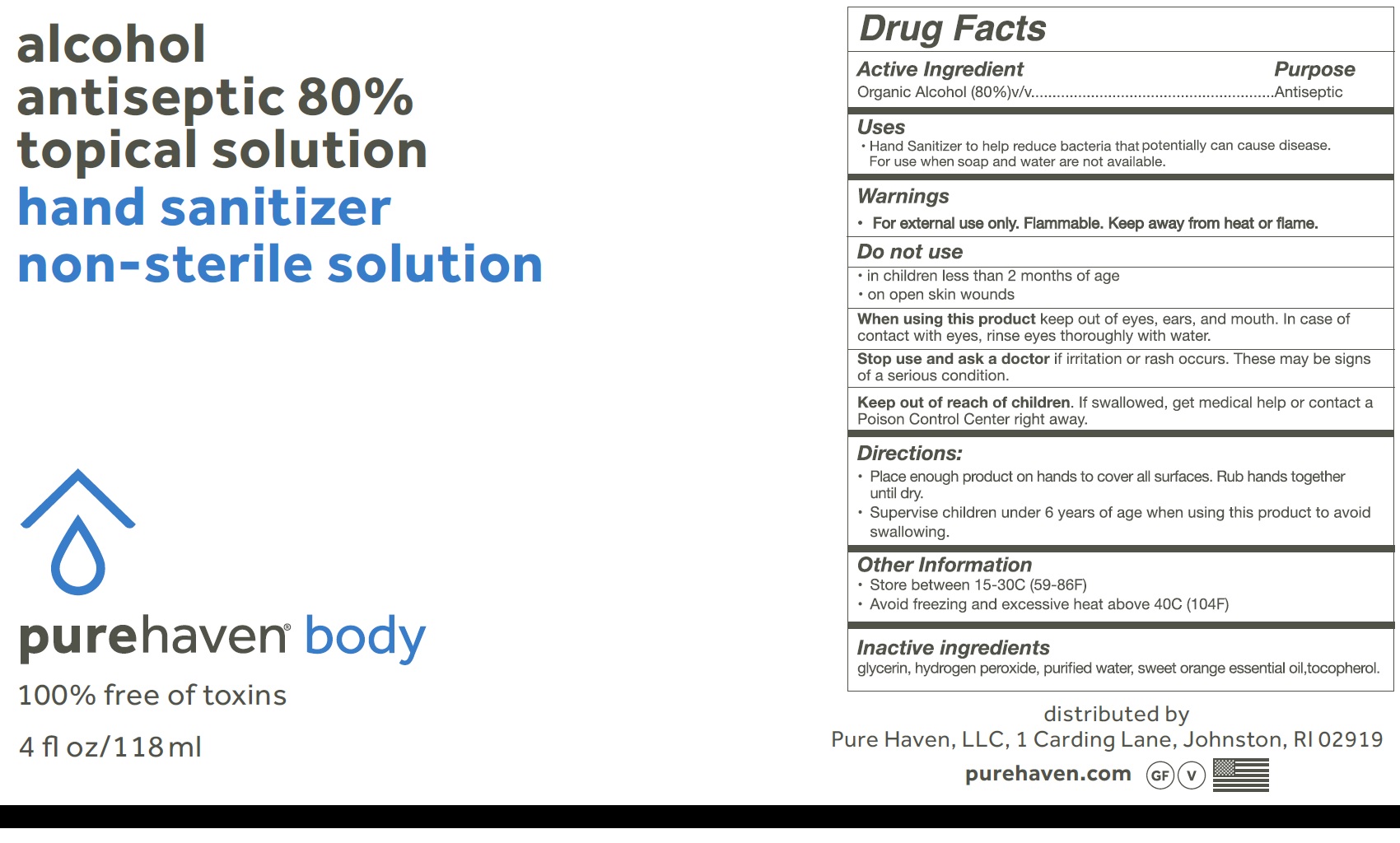 DRUG LABEL: NUBAAL Alcohol Antiseptic 80 Topical Antiseptic Hand Rub Non-sterile
NDC: 51384-001 | Form: GEL
Manufacturer: Botanicals Internacional S.A. de C.V.
Category: otc | Type: HUMAN OTC DRUG LABEL
Date: 20200619

ACTIVE INGREDIENTS: ALCOHOL 0.8 mL/1 mL
INACTIVE INGREDIENTS: TOCOPHEROL; ORANGE OIL; WATER; GLYCERIN; HYDROGEN PEROXIDE

NUBAAL Alcohol Antiseptic 80% Topical Solution Antiseptic Hand Rub Non-sterile Solution

Active ingredient (s)

Organic Alcohol 80% v/v

Purpose

Antiseptic

Use

Hand Sanitizer to help reduce bacteria that potentially can cause disease.

Warnings

For external use only. Flammable. Keep away from heat or flame.

Do not use

- in children less than 2 months of age
- on open skin wounds

When using this product keep out of eyes, ears, and mouth. In case of contact with eyes, rinse eyes thoroughly with water.

Stop use and ask a doctor if irritation or rash occurs. These may be signs of a serious condition.

Keep out of reach of children. If swallowed, get medical help or contact a Poison Control Center right away.

Directions

- Place enough product on hands to cover all surfaces. Rub hands together until dry.
- Supervise children under 6 years of age when using this product to avoid swallowing.

Other information

- store between 15-30oC (59-86oF)
- Avoid freezing and excessive heat above 40oC (104oF)

Inactive ingredients

Glycerin, hydrogen pyroxide, purified water, Aloe vera extract, sweet orange essential oil, tocopherol